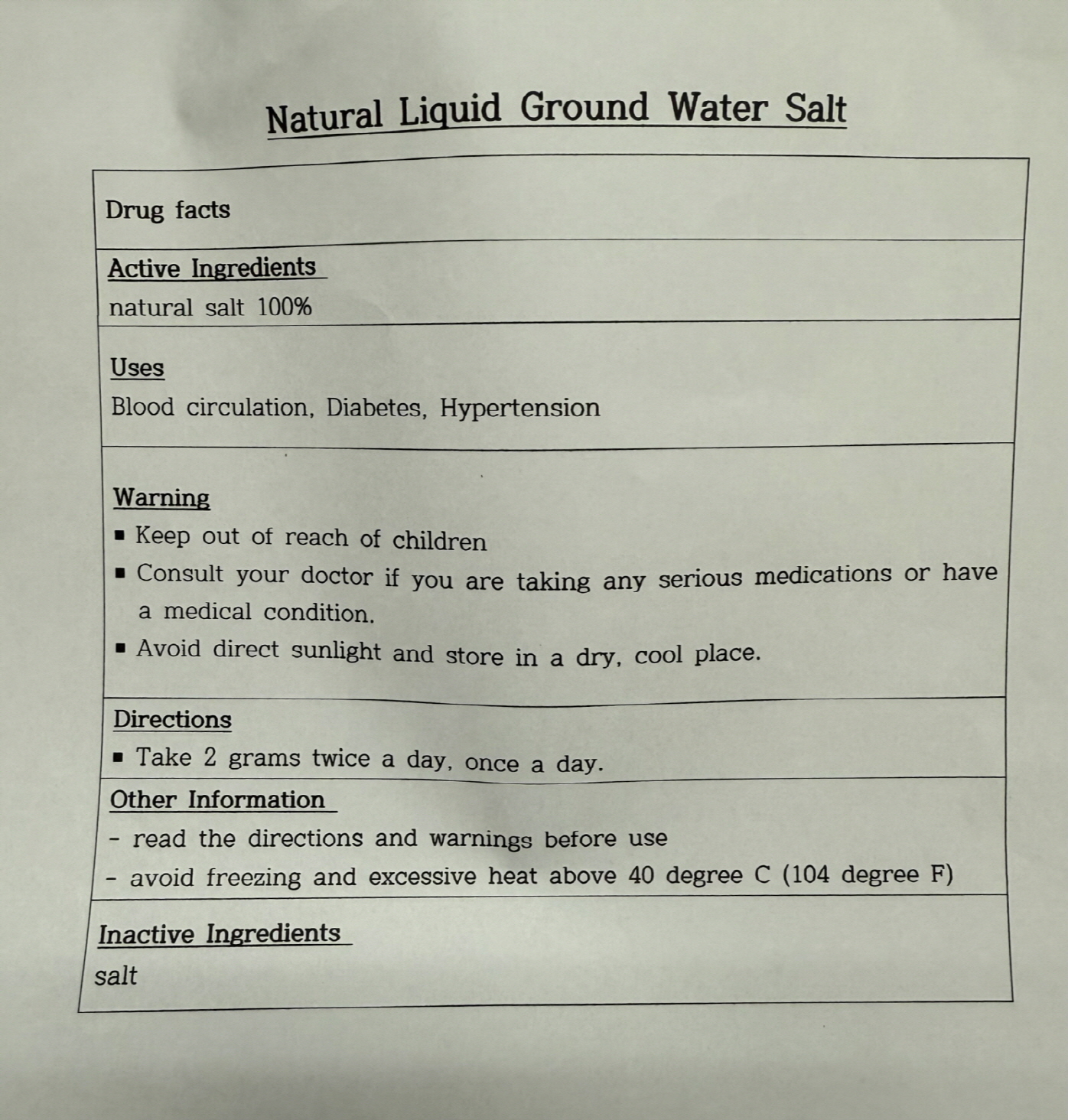 DRUG LABEL: NATURAL LIQUIDGROUND WATER SALT
NDC: 87034-0001 | Form: POWDER
Manufacturer: K-LA-KO Co.,LTD
Category: otc | Type: HUMAN OTC DRUG LABEL
Date: 20250819

ACTIVE INGREDIENTS: SODIUM CHLORIDE 100 g/100 g
INACTIVE INGREDIENTS: WATER

Drug Facts

ACTIVE INGREDIENT

NATURAL SALT 100%

INACTIVE INGREDIENT

N/A

PURPOSE

Blood circulation, Diabetes, Hypertension

keep out of reach of the children

INDICATIONS AND USAGE

Take 2 grams twice a day, once a day

WARNINGS

Consult your doctor if you are taking any serious medication or have a medical condition

Avoid direct sunlight and store in a dry, cool place.

Read the directions and warnings before use.

Avoid freezing and excessive heat abouve 40 degree C (104 degree F)

DOSAGE AND ADMINISTRATION

topical use only